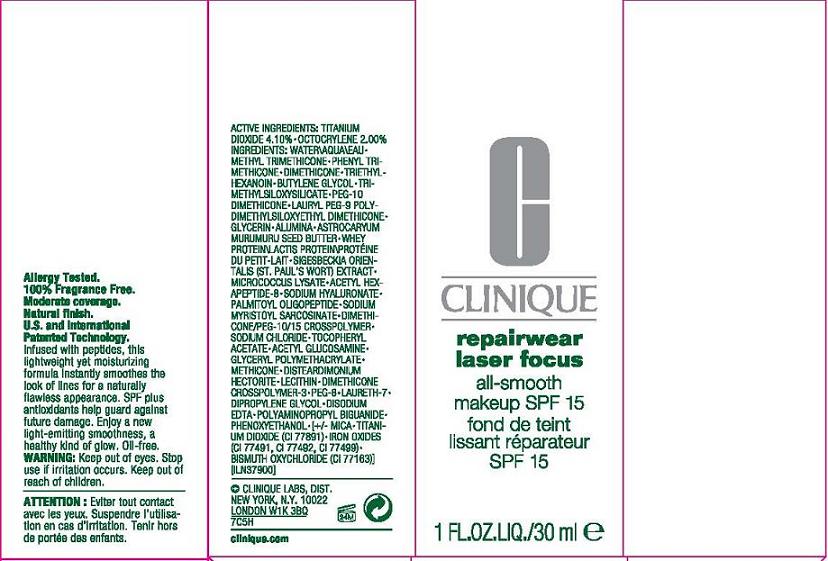 DRUG LABEL: REPAIRWEAR
NDC: 49527-011 | Form: LOTION
Manufacturer: CLINIQUE LABORATORIES INC
Category: otc | Type: HUMAN OTC DRUG LABEL
Date: 20110623

ACTIVE INGREDIENTS: TITANIUM DIOXIDE 2.9 mL/100 mL; OCTOCRYLENE 2.0 mL/100 mL
INACTIVE INGREDIENTS: WATER; METHYL TRIMETHICONE; PHENYL TRIMETHICONE; DIMETHICONE; TRIETHYLHEXANOIN; BUTYLENE GLYCOL; GLYCERIN; ALUMINUM OXIDE; ASTROCARYUM MURUMURU SEED BUTTER; WHEY; ACETYL HEXAPEPTIDE-3; HYALURONATE SODIUM; PALMITOYL OLIGOPEPTIDE; SODIUM MYRISTOYL GLUTAMATE; SODIUM CHLORIDE; ALPHA-TOCOPHEROL ACETATE; LECITHIN, SOYBEAN; POLYETHYLENE GLYCOL 500; LAURETH-7; DIPROPYLENE GLYCOL; EDETATE DISODIUM; POLYAMINOPROPYL BIGUANIDE; PHENOXYETHANOL; MICA; FERRIC OXIDE RED; FERROSOFERRIC OXIDE; FERRIC OXIDE YELLOW; BISMUTH OXYCHLORIDE

ACTIVE INGREDIENT

active ingredients: titanium dioxide 2.90% [] octocrylene 2.00%

INACTIVE INGREDIENT

inactive ingredients: water [] methyl trimethicone [] phenyl trimethicone [] dimethicone [] triethylhexanoin [] butylene glycol [] trimethylsiloxysilicate [] peg-10 dimethicone [] lauryl peg-9 polydimethylsiloxyethyl dimethicone [] glycerin [] alumina [] astrocaryum murumuru seed butter [] whey protein\lactis protein\protéine du petit-lait [] sigesbeckia orientalis (st. paul's wort) extract [] micrococcus lysate [] acetyl hexapeptide-8 [] sodium hyaluronate [] palmitoyl oligopeptide [] sodium myristoyl sarcosinate [] dimethicone/peg-10/15 crosspolymer [] sodium chloride [] tocopheryl acetate [] acetyl glucosamine [] glyceryl polymethacrylate [] methicone [] disteardimonium hectorite [] lecithin [] dimethicone crosspolymer-3 [] peg-8 [] laureth-7 [] dipropylene glycol [] disodium edta [] polyaminopropyl biguanide [] phenoxyethanol [] [+/- mica [] titanium dioxide (ci 77891) [] iron oxides (ci 77491, ci 77492, ci 77499) [] bismuth oxychloride (ci 77163)]

WARNINGS

warning: keep out of eyes. stop use if irritation occurs. keep out of reach of children

PACKAGE LABEL

principal display panel:

CLINIQUE

REPAIRWEAR

LASERFOCUS

ALL SMOOTH MAKEUP

SPF 15

1 FL OZ LIQ/30 ML
CLINIQUE LABORATORIES INC DIST
NEW YORK, NY 10022